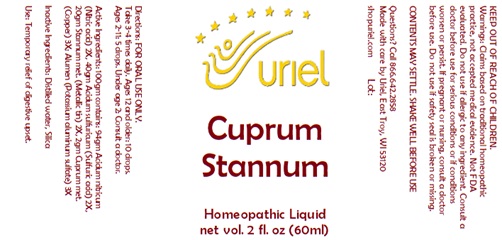 DRUG LABEL: Cuprum Stannum
NDC: 48951-3145 | Form: LIQUID
Manufacturer: Uriel Pharmacy Inc.
Category: homeopathic | Type: HUMAN OTC DRUG LABEL
Date: 20231114

ACTIVE INGREDIENTS: NITRIC ACID 2 [hp_X]/1 mL; SULFURIC ACID 2 [hp_X]/1 mL; TIN 2 [hp_X]/1 mL; COPPER 3 [hp_X]/1 mL; POTASSIUM ALUM 3 [hp_X]/1 mL
INACTIVE INGREDIENTS: WATER; SILICON DIOXIDE

Cuprum Stannum

INDICATIONS AND USAGE

Directions: FOR ORAL USE ONLY.

DOSAGE AND ADMINISTRATION

Take 3-4 times daily. Ages 12 and older: 10 drops. Ages 2-11: 5 drops. Under age 2: Consult a doctor.

ACTIVE INGREDIENT

Active Ingredients: 100gm contains: 94gm Acidum nitricum (Nitric acid) 2X, 40gm Acidum sulfuricum (Sulfuric acid) 2X, 20gm Stannum met. (Metallic tin) 2X, 2gm Cuprum met. (Copper) 3X; Alumen (Potassium aluminum sulfate) 3X

Inactive Ingredients: Distilled water, Silica

PURPOSE

Use: Temporary relief of digestive upset.

KEEP OUT OF REACH OF CHILDREN.

WARNINGS

Warnings: Claims based on traditional homeopathic practice, not accepted medical evidence. Not FDA evaluated. Do not use if allergic to any ingredient. Consult a doctor before use for serious conditions or if conditions worsen or persist. If pregnant or nursing, consult a doctor before use. Do not use if safety seal is broken or missing.

QUESTIONS

Questions? Call 866.642.2858 Made with care by Uriel, East Troy, WI 53120 shopuriel.com